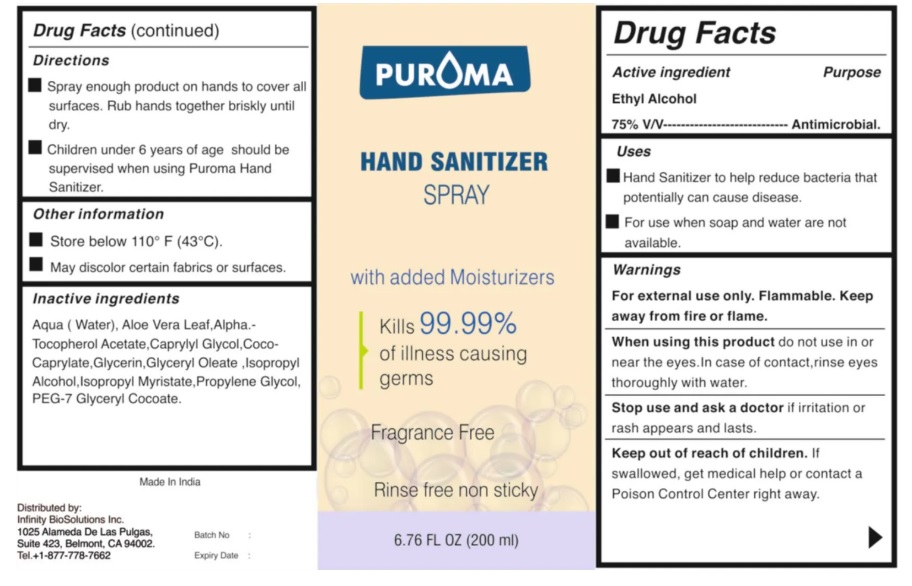 DRUG LABEL: PUROMA Hand Sanitizer Fragrance Free
NDC: 80948-010 | Form: LIQUID
Manufacturer: ZENITH MICRO CONTROL
Category: otc | Type: HUMAN OTC DRUG LABEL
Date: 20231214

ACTIVE INGREDIENTS: ALCOHOL 75 mL/100 mL
INACTIVE INGREDIENTS: WATER; ISOPROPYL ALCOHOL; GLYCERIN; ISOPROPYL MYRISTATE; ALPHA-TOCOPHEROL ACETATE; CAPRYLYL GLYCOL; ALOE VERA LEAF; PROPYLENE GLYCOL; COCO-CAPRYLATE; GLYCERYL OLEATE; PEG-7 GLYCERYL COCOATE

Active ingredient

Ethyl alcohol 75% V/V

Purpose

Antimicrobial.

Uses

Hand Sanitizer to help reduce bacteria on skin that potentially can cause disease.

For use when soap and water are not available.

Warnings

• Flammable. Keep away from fire or flame.
• When using this product do not use in or near the eyes. In case of contact, rinse eyes thoroughly with water.
• Stop use and ask a doctor if irritation or rash appears and lasts.

Keep out of reach of children

If swallowed, get medical help or contact a poison control center right away.

Directions

Spray enough product on hands to cover all surfaces. Rub hands together briskly until dry.

Children under 6 years of age should be supervised when using Puroma hand sanitizer

Inactive ingredients

Water,Isopropyl Alcohol ,Glycerin, Isopropyl Myristate, Alpha.- Tocopherol Acetate , Caprylyl Glycol, Aloe Vera Leaf, Propylene Glycol, Coco-Caprylate , PEG-7 Glyceryl Cocoate, Glyceryl Oleate

Other information

• Store below 110°F (43°C).
• May discolor certain fabrics or surfaces.